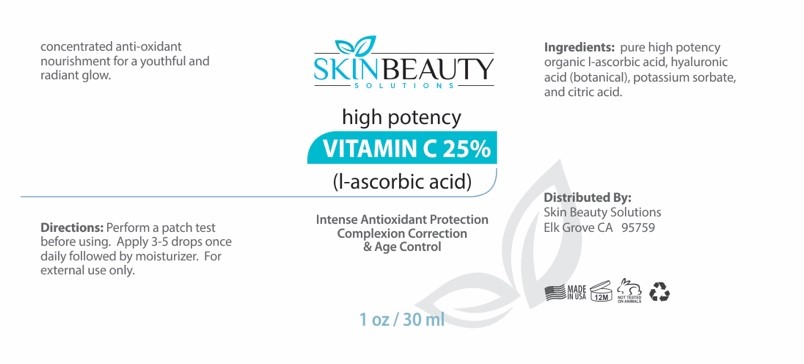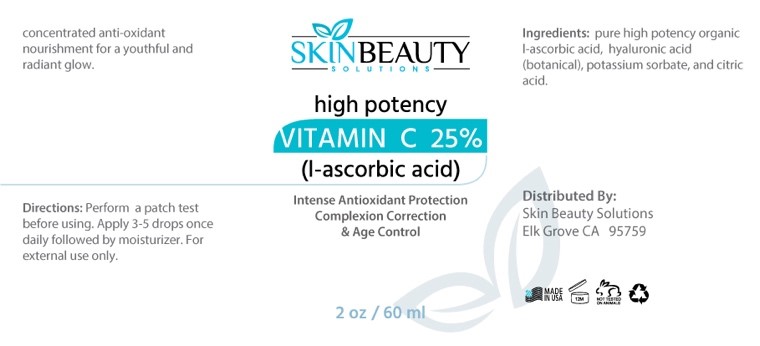 DRUG LABEL: Vitamin C 25% (L- Ascorbic Acid)
NDC: 84785-0054 | Form: SOLUTION
Manufacturer: Gazebo Wellness SKIN LLC
Category: otc | Type: HUMAN OTC DRUG LABEL
Date: 20241218

ACTIVE INGREDIENTS: HYALURONIC ACID 0.3 mg/30 mL; ASCORBIC ACID 0.3 mg/30 mL
INACTIVE INGREDIENTS: POTASSIUM SORBATE; CITRIC ACID ACETATE

DOSAGE AND ADMINISTRATION

concentrated anti-oxidant nourishment for a youthful and radiant glow.

WARNINGS

Directions: Perform a patch test before using. Apply 3-5 drops once daily followed by moisturizer. For external use only.

Inactive ingredients: Potassium Sorbate, Citric Acid.

INDICATIONS AND USAGE

Directions: Perform a patch test before using. Apply 3-5 drops once daily followed by moisturizer. For external use only.

keep out of reach of children

PURPOSE

SKINBEAUTY
SOLUTION
high potency VITAMIN C 25% (l-ascorbic acid)
Intense Antioxidant Protection Complexion Correction & Age Control

Distributed By: Skin Beauty Solutions Elk Grove CA 95759

Active ingredients: L-Ascorbic Acid, Hyaluronic Acid (Botanical).

PACKAGE LABEL

Content of labeling